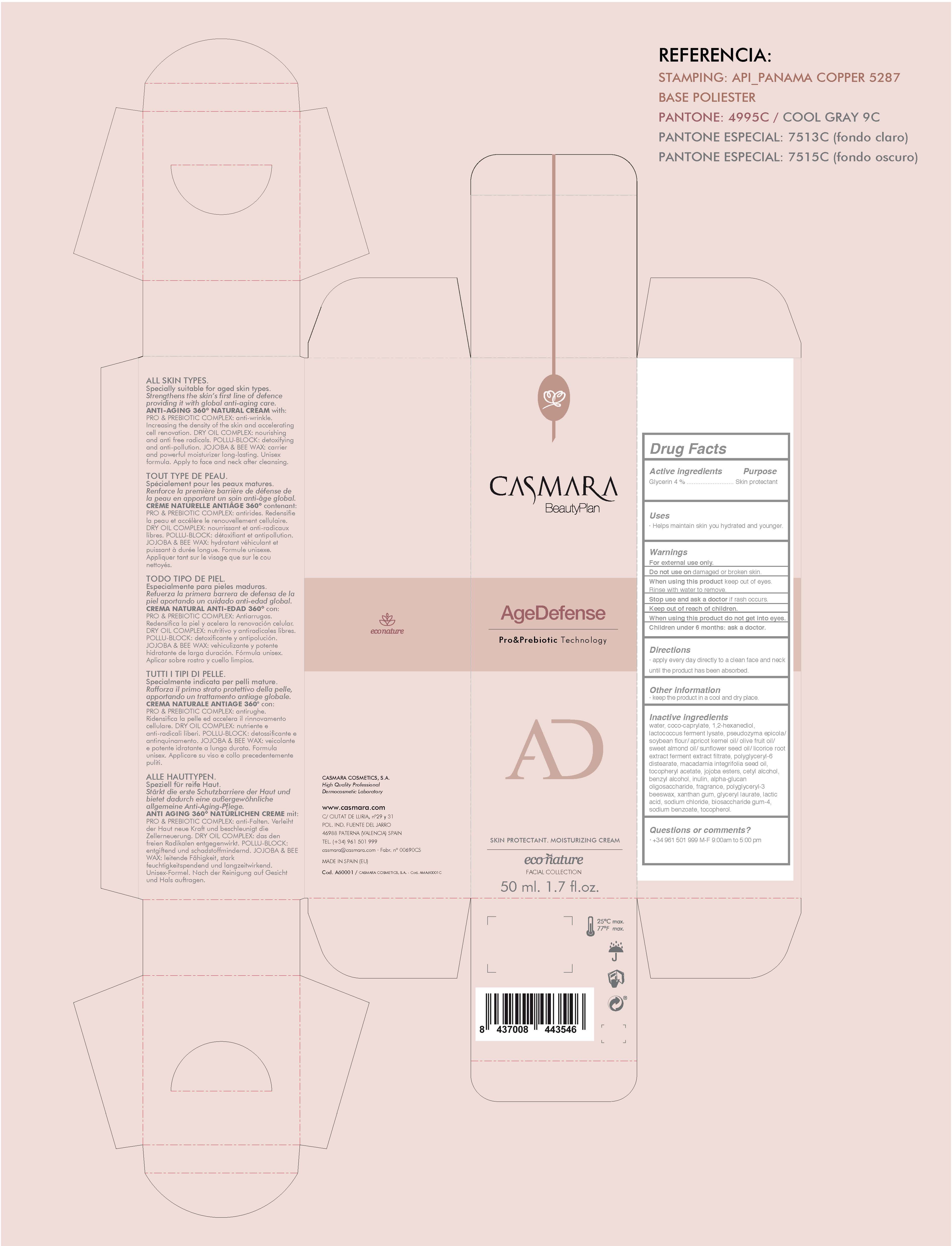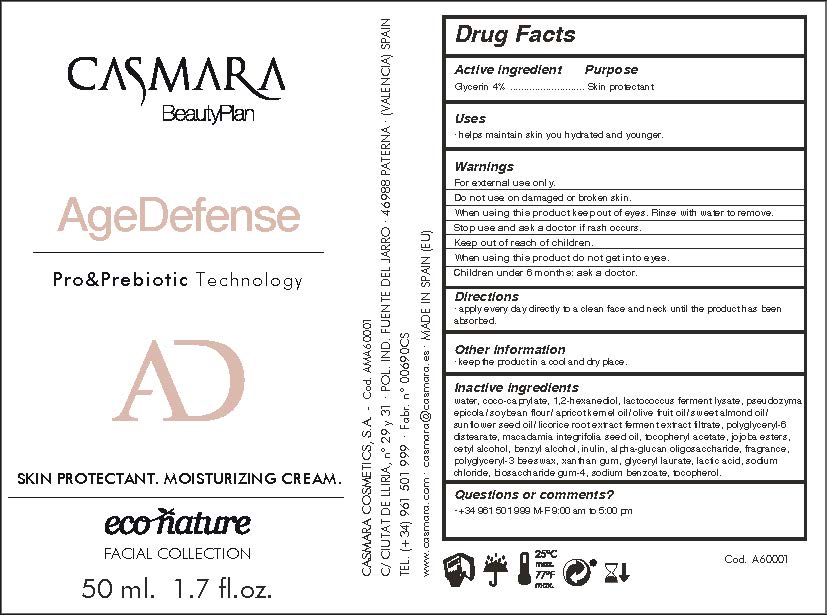 DRUG LABEL: Age Defense Pro Prebiotic Technology Econature
NDC: 20151-104 | Form: CREAM
Manufacturer: Casmara Cosmetics, SA
Category: otc | Type: HUMAN OTC DRUG LABEL
Date: 20170410

ACTIVE INGREDIENTS: GLYCERIN 4 mg/1 mL
INACTIVE INGREDIENTS: YELLOW WAX 0.4 mg/1 mL; LACTOCOCCUS LACTIS 2.97 mg/1 mL; YEAST, UNSPECIFIED 2.5 mg/1 mL; XANTHAN GUM 0.35 mg/1 mL; TOCOPHEROL 0.001 mg/1 mL; 1,2-HEXANEDIOL 3.5 mg/1 mL; LICORICE 2.2 mg/1 mL; POLYGLYCERYL-6 DISTEARATE 2.2 mg/1 mL; MACADAMIA OIL 1.99 mg/1 mL; WATER 62.058 mg/1 mL; ALPHA-TOCOPHEROL ACETATE 1 mg/1 mL; JOJOBA OIL 1 mg/1 mL; CETYL ALCOHOL 0.9 mg/1 mL; BENZYL ALCOHOL 0.855 mg/1 mL; INULIN 0.8 mg/1 mL; .ALPHA.-GLUCAN OLIGOSACCHARIDE 0.7 mg/1 mL; GLYCERYL LAURATE 0.099 mg/1 mL; LACTIC ACID 0.03 mg/1 mL; SODIUM CHLORIDE 0.015 mg/1 mL; BIOSACCHARIDE GUM-4 0.012 mg/1 mL; SODIUM BENZOATE 0.01 mg/1 mL; COCO-CAPRYLATE 14 mg/1 mL

Age Defense Pro Prebiotic Technology. Econature

ACTIVE INGREDIENTS PURPOSE

Glycerin 4%.................... Skin Protectant

Warnings

For external use only.

Do not use on damaged or broken skin.

When using this product keep our of the eyes. Rinse with water to remove.

Stop use and ask a doctor if rash occurs.

Keep out of reach of children.

Whhen using this product do not get into eyes.

Children under 6 months: as a doctor.

WARNINGS

Stop use and ask a doctor if rash occurs

Children under 6 months: ask a doctor

Warnings

Keep out of reach of children

Questions or comments?

+ 34 961 501 999 M-F 9:00 am to 5:00 pm

Other Information

. keep the product in a cool and dry place

Directions

. apply to clean face and neck until the product has been absorbed.

DOSAGE AND ADMINISTRATION

. apply to clean face and neck until the product has been absorbed.

Uses

. helps maintain the sky hydrated and younger

Inactive Ingredients

Aqua (Water), Coco-caprylate,1,2-hexanediol, Lactococcus ferment lysate, Pseudozyma epicola/soybean flour/apricot kernel oil/ olive fruit oil/ sweet almond oil/ sunflower seed oil/ licorice root extract ferment extract filtrate, Polyglyceryl-distearate, Macadamia integrifolia seed oil, Tocopheryl acetate, Jojoba esters, Cetyl alcohol, Benzyl alcohol, Inulin, Alpha-glucan oligosaccharide, Parfum (Fragrance), Polyglyceryl-3 beeswax, Xanthan gum, Glyceryl laurate, Lactic acid, Sodium chloride, Biosaccharide gum-4 , Sodium benzoate, Tocopherol

Uses

. helps maintain the sky hydrated and younger